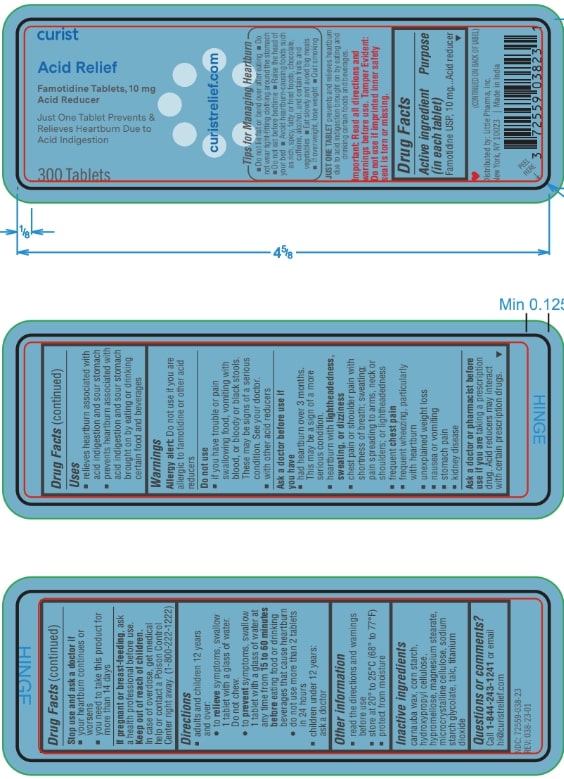 DRUG LABEL: Famotidine
NDC: 72559-038 | Form: TABLET
Manufacturer: Little Pharma, Inc.
Category: otc | Type: HUMAN OTC DRUG LABEL
Date: 20250705

ACTIVE INGREDIENTS: FAMOTIDINE 10 mg/10 mg
INACTIVE INGREDIENTS: TALC; HYDROXYPROPYL CELLULOSE, UNSPECIFIED; MICROCRYSTALLINE CELLULOSE 102; SODIUM STARCH GLYCOLATE TYPE A POTATO; STARCH, CORN; MICROCRYSTALLINE CELLULOSE 101; HYPROMELLOSE 2910 (5 MPA.S); HYPROMELLOSE 2910 (15 MPA.S); TITANIUM DIOXIDE; MAGNESIUM STEARATE; CARNAUBA WAX

Tips for Managing Heartburn

- Do not lie flat or bend over after eating
- Do not wear tight fitting clothing around th estomach
- Do not eat before bedtime
- Raise the head of your bed
- Avoid heartburn-causing foods such as rich, spicy, fatty or fried foods, chocolate, caffeine, alcohol, and certain fruits and vegetables

Just One Tablet prevents and relieves heartburn die to acid indigestion brough on by leating and drinking certain foods and beverages

Important: Read all directions and warnings before use. Tamper Evident: Do not use if imprented inner safety seal is torn or missing

Drug Facts

Active Ingredient (in each tablet)

Famotidine USP 10mg

PURPOSE

Acid reducer

INDICATIONS AND USAGE

- relieves heartburn associated with acid indigestion and sour stomach
- prevents heartburn associated with acid indigestion and sour stomach brough on by eating or drinking certain food and beverages

WARNINGS

Alergy Alert

Do not us if allergic to Famotidine or other acid reducers

Do Not Use

- if you have trouble or pain swallowing food, vomiting with blood, or bloody or black stools. These may be signs of a serious condition. See your doctor
- with other acid reducers

Ask a doctor before use if you have

- had heartburn over 3 months. This may be a sign of a more serious condition,
- heartburn with lightheadedness, sweating, or dizziness
- chest pain or shoulder pain with shortness of breath; sweating; pain spreading to arms, neck or shoulders; or lightheadedness
- frequent chest pain
- frequent wheezing, particularly with heartburn
- unexplained weight loss
- nausea or vomiting
- stomach pain
- kidney disease

Ask a doctor or pharmacist before use if you are taking a prescription drug. Acid reducers may interact with certain prescription drugs.

Stop use and ask a doctor if

- your heartburn continues or worsens
- you need to take this product for more than 14 days

PREGNANCY OR BREAST FEEDING

If pregnant or breast-feeding, ask a health professional before use.

Keep out of reach of children.

in case of overdose, get medical help or contact a Poison Contol Center right away. (1-800-222-1222)

Directions

- adults and children 12 years and over:
- to relieve symtoms, swallow 1 tablet with a glass of water. Do not chew.
- to prevent symptoms, swallow 1 tablet with a glass of water at any time from 15 to 60 minutes before eating food or drinking beverages that cause heartburn
- do not use more than 2 tablets in 24 hours
- children under 12 years: ask a doctor

Other Information

- read the directions and warnings before use
- store at 20º to 25ºC (68º to 77ºF)
- protect from moisture

INACTIVE INGREDIENT

carnuba wax, corn starch, hydroxypropyl cellulose, hypromellose, magnesium stearate, microcrystalline cellulose, sodium starch glycolate, talc, titanium dioxide

Questions or comments?

Call 1-844-243-1241 or email hi@curistrelief.com

PACKAGE LABEL

curist

Acid Relief

Famotidine Tablets, 10mg

Acid Reducer

Just One Tablet Prevents & Relieves Heartburn Dut to Acid Indigestion

300 Tablets